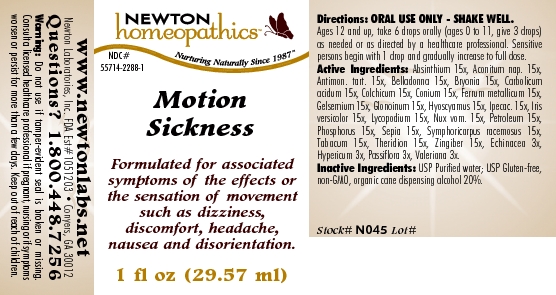 DRUG LABEL: Motion Sickness 
NDC: 55714-2288 | Form: LIQUID
Manufacturer: Newton Laboratories, Inc.
Category: homeopathic | Type: HUMAN OTC DRUG LABEL
Date: 20110301

ACTIVE INGREDIENTS: Wormwood 15 [hp_X]/1 mL; Aconitum Napellus 15 [hp_X]/1 mL; Antimony Potassium Tartrate 15 [hp_X]/1 mL; Atropa Belladonna 15 [hp_X]/1 mL; Bryonia Alba Root 15 [hp_X]/1 mL; Phenol 15 [hp_X]/1 mL; Colchicum Autumnale Bulb 15 [hp_X]/1 mL; Conium Maculatum Flowering Top 15 [hp_X]/1 mL; Iron 15 [hp_X]/1 mL; Gelsemium Sempervirens Root 15 [hp_X]/1 mL; Nitroglycerin 15 [hp_X]/1 mL; Hyoscyamus Niger 15 [hp_X]/1 mL; Ipecac 15 [hp_X]/1 mL; Iris Versicolor Root 15 [hp_X]/1 mL; Lycopodium Clavatum Spore 15 [hp_X]/1 mL; Strychnos Nux-vomica Seed 15 [hp_X]/1 mL; Kerosene 15 [hp_X]/1 mL; Phosphorus 15 [hp_X]/1 mL; Sepia Officinalis Juice 15 [hp_X]/1 mL; Symphoricarpos Albus Fruit 15 [hp_X]/1 mL; Tobacco Leaf 15 [hp_X]/1 mL; Theridion Curassavicum 15 [hp_X]/1 mL; Ginger 15 [hp_X]/1 mL; Echinacea, Unspecified 3 [hp_X]/1 mL; Hypericum Perforatum 3 [hp_X]/1 mL; Passiflora Incarnata Flowering Top 3 [hp_X]/1 mL; Valerian 3 [hp_X]/1 mL
INACTIVE INGREDIENTS: Alcohol

Motion Sickness

INDICATIONS & USAGE SECTION

Motion Sickness Formulated for associated symptoms of the effects or the sensation of movement such as dizziness, discomfort, headache, nausea and disorientation.

DOSAGE & ADMINISTRATION SECTION

Directions: ORAL USE ONLY - SHAKE WELL. Ages 12 and up, take 6 drops orally (ages 0 to 11, give 3 drops) as needed or as directed by a healthcare professional. Sensitive persons begin with 1 drop and gradually increase to full dose.

OTC - ACTIVE INGREDIENT SECTION

Absinthium 15x, Aconitum nap. 15x, Antimon. tart. 15x, Belladonna 15x, Bryonia 15x, Carbolicum acidum 15x, Colchicum 15x, Conium 15x, Ferrum metallicum 15x, Gelsemium 15x, Glonoinum 15x, Hyoscyamus 15x, Ipecac. 15x, Iris versicolor 15x, Lycopodium 15x, Nux vom. 15x, Petroleum 15x, Phosphorus 15x, Sepia 15x, Symphoricarpus racemosus 15x, Tabacum 15x, Theridion 15x, Zingiber 15x, Echinacea 3x, Hypericum 3x, Passiflora 3x, Valeriana 3x.

OTC - PURPOSE SECTION

Formulated for associated symptoms of the effects or the sensation of movement such as dizziness, discomfort, headache, nausea and disorientation.

INACTIVE INGREDIENT SECTION

Inactive Ingredients: USP Purified Water; USP Gluten-free, non-GMO, organic cane dispensing alcohol 20%.

QUESTIONS SECTION

www.newtonlabs.net Newton Laboratories, Inc. FDA Est # 1051203 - Conyers, GA 30012
Questions? 1.800.448.7256

WARNINGS SECTION

Warning: Do not use if tamper - evident seal is broken or missing. Consult a licensed healthcare professional if pregnant, nursing or if symptoms worsen or persist for more than a few days. Keep out of reach of children.

OTC - PREGNANCY OR BREAST FEEDING SECTION

Consult a licensed healthcare professional if pregnant, nursing or if symptoms worsen or persist for more than a few days.

OTC - KEEP OUT OF REACH OF CHILDREN SECTION

Keep out of reach of children.